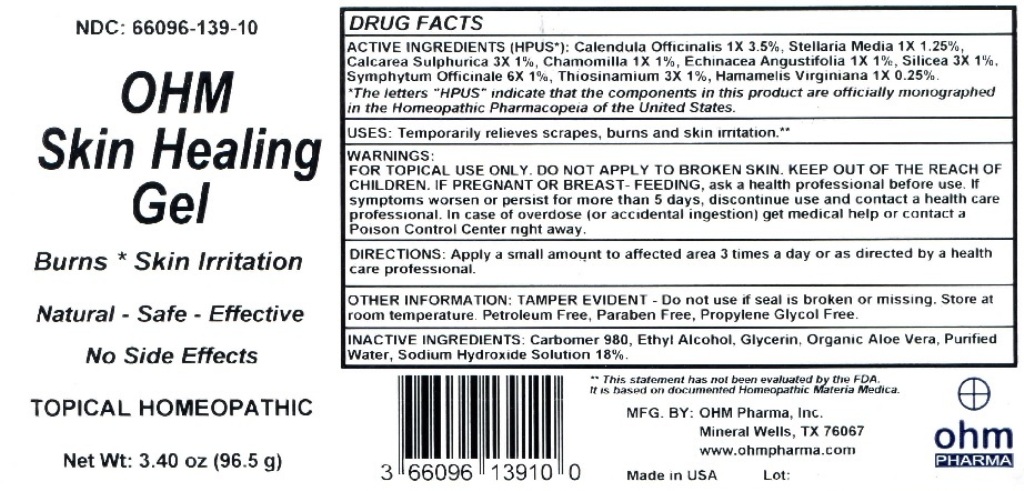 DRUG LABEL: OHM Skin Healing Gel
NDC: 66096-139 | Form: GEL
Manufacturer: OHM PHARMA INC.
Category: homeopathic | Type: HUMAN OTC DRUG LABEL
Date: 20211229

ACTIVE INGREDIENTS: CALENDULA OFFICINALIS FLOWERING TOP 1 [hp_X]/96.5 g; STELLARIA MEDIA 1 [hp_X]/96.5 g; CALCIUM SULFATE ANHYDROUS 3 [hp_X]/96.5 g; MATRICARIA RECUTITA 1 [hp_X]/96.5 g; ECHINACEA ANGUSTIFOLIA 1 [hp_X]/96.5 g; SILICON DIOXIDE 3 [hp_X]/96.5 g; COMFREY ROOT 6 [hp_X]/96.5 g; ALLYLTHIOUREA 3 [hp_X]/96.5 g; HAMAMELIS VIRGINIANA ROOT BARK/STEM BARK 1 [hp_X]/96.5 g
INACTIVE INGREDIENTS: CARBOMER HOMOPOLYMER TYPE C (ALLYL PENTAERYTHRITOL CROSSLINKED); ALCOHOL; GLYCERIN; ALOE VERA LEAF; WATER; SODIUM HYDROXIDE

OHM Skin Healing Gel

ACTIVE INGREDIENT

ACTIVE INGREDIENTS (HPUS*): Calendula Officinalis 1X 3.5%, Stellaria Media 1X 1.25%, Calcarea Sulphurica 3X 1%, Chamomilla 1X 1%, Echinacea Angustfolia 1X 1%, Silicea 3X 1%, Symphytum Officinale 6X 1%, Thiosinamium 3X 1%, Hamamelis Virginiana 1X 0.25%.

*The letters "HPUS" indicate that the components in this product are officially monographed in the Homeopathic Pharmacopeia of the United States.

INDICATIONS AND USAGE

USES: Temporarily relieves scrapes, burns and skin irritation.**

**This statement has not been evaluated by the FDA. It is based on documented Homeopathic Materia Medica.

WARNINGS

WARNINGS: FOR TOPICAL USE ONLY. DO NOT APPLY TO BROKEN SKIN. IF PREGNANT OR BREAST - FEEDING, ask a health care professional before use. If symptoms worsen or persist for more than 5 days, discontinue use and contact a health care professional. In case of overdose (or accidental ingestion) get medical help or contact a Poison Control Center right away.

- KEEP OUT OF REACH OF CHILDREN

DOSAGE AND ADMINISTRATION

DIRECTIONS: Apply a small amount to affected area 3 times a day or as directed by a health care professional.

OTHER INFORMATION: TAMPER EVIDENT - Do not use if seal is broken or missing. Store at room temperature. Petroleum Free, Paraben Free, Propylene Glycol Free.

INACTIVE INGREDIENT

INACTIVE INGREDIENTS: Carbomer 980, Ethyl Alcohol, Glycerin, Organic Aloe Vera, Purified Water, Sodium Hydroxide Solution 18%.

QUESTIONS

MFG. By: OHM PHARMA, INC. / Mineral Wells, TX 76067
www.ohmpharma.com

PACKAGE LABEL

NDC: 66096-139-10

OHM

SKIN HEALING GEL

Burns *Skin Irritation

Natural - Safe - Effective

TOPICAL HOMEOPATHIC

Net Wt: 3.40oz (96.5g)

Made In Usa

PURPOSE

Burns and Skin Irritation